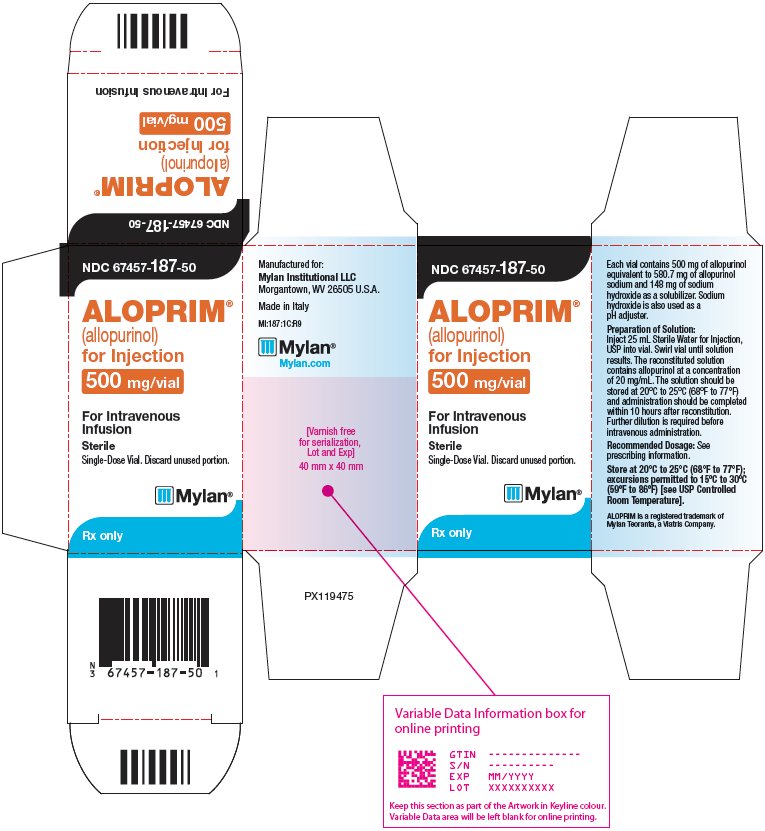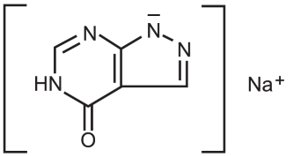 DRUG LABEL: Aloprim
NDC: 67457-187 | Form: INJECTION, POWDER, LYOPHILIZED, FOR SOLUTION
Manufacturer: Mylan Institutional LLC
Category: prescription | Type: HUMAN PRESCRIPTION DRUG LABEL
Date: 20220218

ACTIVE INGREDIENTS: ALLOPURINOL SODIUM 500 mg/25 mL
INACTIVE INGREDIENTS: SODIUM HYDROXIDE 148 mg/25 mL

HIGHLIGHTS OF PRESCRIBING INFORMATION

These highlights do not include all the information needed to use ALOPRIM safely and effectively. See full prescribing information for ALOPRIM.
ALOPRIM® (allopurinol) for injection, for intravenous use
Initial U.S. Approval: 1966

1 INDICATIONS AND USAGE

ALOPRIM is a xanthine oxidase inhibitor indicated for the management of adult and pediatric patients with leukemia, lymphoma, and solid tumor malignancies who are receiving cancer therapy which causes elevations of serum and urinary uric acid levels and who cannot tolerate oral therapy. (1)

2 DOSAGE AND ADMINISTRATION

- Recommended Dosage (2.2)

Adult Patients | 200 mg/m^2/day to 400 mg/m^2/day Maximum 600 mg/day
Pediatric Patients | Starting Dose 200 mg/m^2/day; Maximum 400 mg/day

- Recommended Dosage in Adult Patients with Renal Impairment (2.2, 5.2, 8.6)

Creatinine Clearance | Recommended Daily Dose
10 to 20 mL/min | 200 mg/day
Less than 10 mL/min | 100 mg/day
On dialysis | 50 mg every 12 hours, or; 100 mg every 24 hours

3 DOSAGE FORMS AND STRENGTHS

For injection: 500 mg as a white lyophilized powder or cake in a single-dose vial for reconstitution (3)

4 CONTRAINDICATIONS

Known hypersensitivity to allopurinol. (4)

5 WARNINGS AND PRECAUTIONS

- Skin Rash and Hypersensitivity: Discontinue ALOPRIM at the first appearance of skin rash or other signs which may indicate a hypersensitivity reaction. Allopurinol has been associated with serious and sometimes fatal dermatologic reactions. (5.1)
- Renal Function Impairment: Patients with decreased renal function require lower doses of allopurinol. (5.2)
- Hepatotoxicity: If signs and symptoms of hepatotoxicity develop, liver function evaluation should be performed. (5.3)
- Myelosuppression: Bone marrow suppression has been reported with allopurinol. (5.4)
- Drowsiness: Drowsiness has been reported in patients taking ALOPRIM. (5.5)

6 ADVERSE REACTIONS

Most common adverse reactions (incidence > 1%) are skin rash, nausea, vomiting, and renal failure/insufficiency. (6.1)

To report SUSPECTED ADVERSE REACTIONS, contact Mylan at 1-877-446-3679 (1-877-4-INFO-RX) or FDA at 1-800-FDA-1088 or www.fda.gov/medwatch.

7 DRUG INTERACTIONS

- Capecitabine: Avoid the concomitant use of allopurinol (7.2).
- Pegloticase: Discontinue and do not institute allopurinol therapy during treatment with pegloticase (7.2).
- Mercaptopurine or Azathioprine: Reduce mercaptopurine or azathioprine dose as recommended in the respective prescribing information (7.2).
- See full prescribing information for complete list of significant drug interactions (7).

8 USE IN SPECIFIC POPULATIONS

- Pregnancy: May cause fetal harm (8.1).
- Lactation: Advise not to breastfeed (8.2).

FULL PRESCRIBING INFORMATION

1 INDICATIONS AND USAGE

ALOPRIM is indicated for the management of adult and pediatric patients with leukemia, lymphoma, and solid tumor malignancies who are receiving cancer therapy which causes elevations of serum and urinary uric acid levels and who cannot tolerate oral therapy.

2 DOSAGE AND ADMINISTRATION

2.1 Recommended Dosage

Initiate therapy with ALOPRIM 24 to 48 hours before the start of chemotherapy known to cause tumor cell lysis. Additionally, administer fluids sufficient to yield a daily urinary output of at least two liters in adults with a neutral or, preferably, slightly alkaline urine.

The recommended daily dose of ALOPRIM is shown in Table 1. Administer the daily dose as single infusion or in equally divided infusions at 6-, 8-, or 12-hour intervals at a rate appropriate for the volume of infusate.

Table 1: Recommended Daily Dose of ALOPRIM
Adult Patients | 200 mg/m^2/day to 400 mg/m^2/day intravenously Maximum 600 mg/day
Pediatric Patients | Starting Dose 200 mg/m^2/day intravenously; Maximum 400 mg/day

The dosage of ALOPRIM to lower serum uric acid to normal or near-normal varies with the severity of the disease. Monitor serum uric acid levels at least daily and administer ALOPRIM at a dose and frequency to maintain the serum uric acid within the normal range. Discontinue ALOPRIM when the patient is able to take oral therapy or when the risk of tumor lysis has abated.

2.2 Dosage Modifications in Patients with Renal Impairment

Reduce the dose of ALOPRIM in patients with impaired renal function [see Use in Specific Populations (8.6) and Clinical Pharmacology (12.3)]. The recommended dosage reductions of ALOPRIM in adult patients with renal impairment are shown in Table 2.

Table 2: Recommended Daily Dose of ALOPRIM in Adult Patients with Renal Impairment
Creatinine Clearance | Recommended Daily Dose
10 to 20 mL/min | 200 mg/day
Less than 10 mL/min | 100 mg/day
On dialysis | 50 mg every 12 hours, or; 100 mg every 24 hours

Treatment with ALOPRIM has not been studied in pediatric patients with severe renal impairment or on dialysis. For pediatric patients with severe renal impairment or on dialysis, consider the risks and potential benefits before initiating treatment with ALOPRIM [see Warnings and Precautions (5.2) and Use In Specific Populations (8.6)].

2.3 Preparation Instructions

Reconstitue and further dilute ALOPRIM prior to intravenous infusion.

Reconstitution

- Reconstitute each vial of ALOPRIM with 25 mL of Sterile Water for Injection, USP to obtain a concentration of 20 mg/mL of allopurinol.
- Inspect the reconstituted solution for discoloration and particulate matter. The reconstituted solution should appear as a clear, almost colorless solution with no more than a slight opalescence. Do not use if the reconstituted solution contains particulate matter or discoloration is present.

Dilution

- Dilute with 0.9% Sodium Chloride Injection, USP or 5% Dextrose for Injection, USP to obtain a final concentration of less than 6 mg/mL.
- Inspect the diluted solution for particulate matter or discoloration and discard if present.
- If not used immediately, the diluted ALOPRIM solution can be stored at 20° to 25°C (68° to 77°F) for up to 10 hours after initial reconstitution. The storage includes time for infusion. Do not refrigerate the reconstituted and/or diluted product.
- If stored, the administration should be completed within 10 hours after reconstitution.
- Discard unused portion.

2.4 Administration Instructions

Do not mix ALOPRIM with or administer it through the same intravenous port as agents which are incompatible in solution with ALOPRIM. The following table lists drugs that are known to be physically incompatible in solution with ALOPRIM.

Table 3: Drugs That Are Physically Incompatible in Solution with ALOPRIM
Amikacin sulfate | Hydroxyzine HCl
Amphotericin B | Idarubicin HCl
Carmustine | Imipenem-cilastatin sodium
Cefotaxime sodium | Mechlorethamine HCl
Chlorpromazine HCl | Meperidine HCl
Cimetidine HCl | Metoclopramide HCl
Clindamycin phosphate | Methylprednisolone sodium succinate
Cytarabine | Minocycline HCl
Dacarbazine | Nalbuphine HCl
Daunorubicin HCl | Ondansetron HCl
Diphenhydramine HCl | Prochlorperazine edisylate
Doxorubicin HCl | Promethazine HCl
Doxycycline hyclate | Sodium bicarbonate
Droperidol | Streptozocin
Floxuridine | Tobramycin sulfate
Gentamicin sulfate | Vinorelbine tartrate
Haloperidol lactate

3 DOSAGE FORMS AND STRENGTHS

For Injection: 500 mg of allopurinol as a sterile, white lyophilized powder or cake in a single-dose vial for reconstitution.

4 CONTRAINDICATIONS

ALOPRIM is contraindicated in patients with a history of severe reaction to any formulation of allopurinol.

5 WARNINGS AND PRECAUTIONS

5.1 Skin Rash and Hypersensitivity

Serious and sometimes fatal dermatologic reactions, including toxic epidermal necrolysis (TEN), Stevens-Johnson syndrome (SJS), and drug reaction with eosinophilia and systemic symptoms (DRESS) have been reported in patients taking allopurinol [see Adverse Reactions (6.1)]. These reactions occur in approximately 5 in 10,000 (0.05%) patients taking allopurinol. Other serious hypersensitivity reactions that have been reported include exfoliative, urticarial and purpuric lesions; generalized vasculitis; and irreversible hepatotoxicity. Discontinue ALOPRIM at the first appearance of skin rash or other signs which may indicate a hypersensitivity reaction.

The HLA-B*58:01 allele is a genetic marker for severe skin reactions indicative of hypersensitivity to allopurinol. Patients who carry the HLA-B*58:01 allele are at a higher risk of allopurinol hypersensitivity syndrome (AHS), but hypersensitivity reactions have been reported in patients who do not carry this allele. The frequency of this allele is higher in individuals of African, Asian (e.g., Han Chinese, Korean, Thai), and Native Hawaiian/Pacific Islander ancestry [see Clinical Pharmacology (12.5)]. The use of ALOPRIM is not recommended in HLA-B*58:01 positive patients unless the benefits clearly outweigh the risks.

Prior to starting ALOPRIM, consider testing for the HLA-B*58:01 allele in genetically at-risk populations. Screening is generally not recommended in patients from populations in which the prevalence of HLA-B*58:01 is low, or in current allopurinol users, as the risk of SJS/TEN/DRESS is largely confined to the first few months of therapy, regardless of HLA-B*58:01 status.

Hypersensitivity reactions to ALOPRIM may be increased in patients with decreased renal function receiving thiazide diuretics and ALOPRIM concurrently. In addition, concomitant use of the following drugs may increase the risk of skin rash, which may be severe: bendamustine, thiazide diuretics, ampicillin and amoxicillin [see Drug Interactions (7.1)]. Patients should stop ALOPRIM and seek medical attention if they develop a rash.

5.2 Renal Function Impairment

Treatment with ALOPRIM may result in renal impairment due to formation of xanthine calculi or due to precipitation of urates in patients receiving concomitant uricosuric agents. Patients with pre-existing renal disease, including renal impairment or history of kidney stones, may be at increased risk for worsening renal impairment due to xanthine calculi or precipitation of urates while receiving treatment with ALOPRIM.

Monitor serum creatinine at least daily during the early stages of allopurinol administration. Maintain fluid intake sufficient to yield a urinary output of at least 2 liters per day in adults. In patients with severely impaired renal function or increase in uric acid concentration associated with decreased urate clearance, reduce the dosage of ALOPRIM [see Use In Specific Populations (8.6) and Dosage and Administration (2.1, 2.2)].

5.3 Hepatotoxicity

Cases of reversible clinical hepatotoxicity have been noted in patients taking oral allopurinol. In some patients, asymptomatic rises in serum alkaline phosphatase or serum transaminase have been observed. If anorexia, weight loss, or pruritus develop in patients on allopurinol, evaluate liver enzymes. In patients with pre-existing liver disease, monitor liver enzymes periodically during the early stages of therapy. Discontinue ALOPRIM in patients with elevated liver enzymes.

5.4 Myelosuppression

Myelosuppression, manifested by anemia, leukopenia or thrombocytopenia, has been reported in patients receiving allopurinol [see Adverse Reactions (6.1)]. The cytopenias have occurred from as early as 6 weeks to as late as 6 years after the initiation of allopurinol therapy. Discontinue use of ALOPRIM in patients with unexplained cytopenias. Concomitant use with allopurinol with cytotoxic drugs associated with myelosuppression may increase the risk of myelosuppression. Monitor blood counts more frequently [see Drug Interactions (7)].

Concomitant use with allopurinol increases the exposure of either mercaptopurine or azathioprine which may increase the risk of myelosuppression. Reduce the dosage of mercaptopurine or azathioprine as recommended in the respective prescribing information when used concomitantly with ALOPRIM. [see Drug Interactions (7)].

5.5 Drowsiness

Drowsiness has been reported in patients taking ALOPRIM [see Adverse Reactions (6.1)]. Advise patients to avoid operation of automobiles or other dangerous machinery and activities made hazardous by decreased alertness when starting ALOPRIM or increasing the dose until they know how the drug affects them. Advise patients that the central nervous system depressant effects of ALOPRIM may be additive to those of alcohol and other CNS depressants.

6 ADVERSE REACTIONS

The following clinically significant adverse reactions are described elsewhere in the labeling:

- Skin Rash and Hypersensitivity [see Warnings and Precautions (5.1)]
- Renal Function Impairment [see Warnings and Precautions (5.2)]
- Hepatoxicity [see Warnings and Precautions (5.3)]
- Myelosuppression [see Warnings and Precautions (5.4)]
- Drowsiness [see Warnings and Precautions (5.5)]

6.1 Clinical Trials Experience

Because clinical trials are conducted under widely varying conditions, adverse reaction rates observed in the clinical trials of a drug cannot be directly compared to rates in the clinical trials of another drug and may not reflect the rates observed in practice.

The safety of ALOPRIM was evaluated in an uncontrolled compassionate use study of 1,378 patients with advanced malignancies requiring treatment with cytotoxic chemotherapy and in patients with other serious conditions.

Adverse reactions were reported in 9% (125/1378) of the patients treated with ALOPRIM.

The most common adverse reaction was skin rash. Two patients experience serious adverse reactions (decreased renal function and generalized seizure) and one patient experienced severe diarrhea. Approximately 1.1% of patients experienced allergic adverse reactions (including rash, eosinophilia, local injection site reaction).

A listing of the adverse reactions reported from clinical trials follows:

Incidence Greater Than 1%:

Cutaneous/Dermatologic: rash (1.5%)

Genitourinary: renal failure/insufficiency (1.2%)

Gastrointestinal: nausea (1.3%), vomiting (1.2%)

Incidence Less Than 1%:

Body as a Whole: fever, pain, chills, alopecia, infection, sepsis, enlarged abdomen, mucositis/pharyngitis, blast crisis, cellulitis, hypervolemia

Cardiovascular: heart failure, cardiorespiratory arrest, hypertension, pulmonary embolus, hypotension, decreased venous pressure, flushing, headache, stroke, septic shock, cardiovascular disorder, ECG abnormality, hemorrhage, bradycardia, thrombophlebitis, ventricular fibrillation

Cutaneous/Dermatologic: urticaria, pruritus, local injection site reaction

Gastrointestinal: diarrhea, gastrointestinal bleeding, hyperbilirubinemia, splenomegaly, hepatomegaly, intestinal obstruction, jaundice, flatulence, constipation, liver failure, proctitis

Genitourinary: hematuria, increased creatinine, oliguria, kidney function abnormality, urinary tract infection

Hematologic: leukopenia, marrow aplasia, thrombocytopenia, eosinophilia, neutropenia, anemia, pancytopenia, ecchymosis, bone marrow suppression, disseminated intravascular coagulation

Metabolic: hypocalcemia, hyperphosphatemia, hypokalemia, hyperuricemia, electrolyte abnormality, hypercalcemia, hyperglycemia, hypernatremia, hyponatremia, metabolic acidosis, edema, glycosuria, hyperkalemia, lactic acidosis, water intoxication, hypomagnesemia

Neurologic: seizure, status epilepticus, myoclonus, twitching, agitation, mental status changes, cerebral infarction, coma, dystonia, paralysis, tremor

Pulmonary: respiratory failure/insufficiency, ARDS, increased respiration rate, apnea

Musculoskeletal: arthralgia

Other: hypotonia, diaphoresis, tumor lysis syndrome

7 DRUG INTERACTIONS

Clinically important interactions with the drugs listed below were observed in patients undergoing treatment with an oral allopurinol formulation.

7.1 Drugs Known to Affect the Occurrence of Skin Rash and Hypersensitivity

Concomitant use of the following drugs may increase the risk of skin rash, which may be severe: bendamustine, thiazide diuretics, ampicillin and amoxicillin. Renal impairment may further increase risk with concomitant use of thiazide diuretics [see Warnings and Precautions (5.1) (5.2) and Clinical Pharmacology (12.2)].

Monitor renal function and reduce the dose of ALOPRIM in patients with concomitant thiazide diuretic use and impaired renal function [see Dosage and Administration (2.2)].

Discontinue ALOPRIM at the first appearance of skin rash or other signs which may indicate a hypersensitivity reaction when use concomitantly with these drugs.

7.2 Other Drugs Known to Have Clinically Important Drug Interactions with ALOPRIM

Table 4: Interventions for Clinically Important Drug Interactions with ALOPRIM
Capecitabine
Clinical Impact | Concomitant use with allopurinol may decrease concentration of capecitabine’s active metabolites, which may decrease capecitabine efficacy.
Intervention | Avoid the use of ALOPRIM during treatment with capecitabine.
Cyclosporine
Clinical Impact | Concomitant use of allopurinol increases cyclosporine concentrations which may increase the risk of adverse reactions.
Intervention | Increase frequency of monitoring cyclosporine concentrations as reflected in the prescribing information when used concomitantly with ALOPRIM.
Cytotoxic Agents
Clinical Impact | Concomitant use of allopurinol with cytotoxic agents increases bone marrow suppression among patients with neoplastic disease, except leukemia [see Warnings and Precautions (5.4) and Clinical Pharmacology (12.2)].
Intervention | Blood count monitoring and regular physician follow-up recommended.
Fluorouracil
Clinical Impact | Based on non-clinical data, allopurinol may decrease anti-tumor activity due to suppression of phosphorylation of 5-fluorouracil.
Intervention | Concomitant administration with fluorouracil should be avoided.
Mercaptopurine or Azathioprine
Clinical Impact | Allopurinol inhibits xanthine oxidase mediated metabolism of mercaptopurine and azathioprine. Concomitant use of allopurinol increases the exposure of either mercaptopurine or azathioprine which may increase the risk of their adverse reactions including myelosuppression [see Warnings and Precautions (5.4)].
Intervention | Reduce the dosage of mercaptopurine or azathioprine as recommended in the respective prescribing information.
Pegloticase
Clinical Impact | Concomitant use of ALOPRIM and pegloticase may potentially blunt the rise of serum uric acid levels and increase the risk of pegloticase related anaphylaxis in patients whose uric acid level increase to above 6 mg/dL.
Intervention | Discontinue and do not institute ALOPRIM therapy during treatment with pegloticase.
Theophylline
Clinical Impact | Concomitant use of allopurinol doses greater than or equal to 600 mg/day may decrease the clearance of theophylline.
Intervention | Monitor and adjust theophylline doses as reflected in the prescribing information.
Uricosuric Agents
Clinical Impact | Uricosuric agents increase the excretion of the active allopurinol metabolite oxypurinol. Concomitant use with uricosuric agents decreases oxypurinol exposure which may reduce the inhibition of xanthine oxidase by oxypurinol and increases the urinary excretion of uric acid.
Intervention | Monitor uric acid levels due to the increased chance of hypouricemic effects.
Warfarin
Clinical Impact | Allopurinol may inhibit the metabolism of warfarin, possibly enhancing its anticoagulant effect.
Intervention | Patients on concomitant therapy should be monitored for excessive anticoagulation. The INR should be checked frequently and warfarin dosage adjusted accordingly when allopurinol is added to warfarin therapy.

8 USE IN SPECIFIC POPULATIONS

8.1 Pregnancy

Risk Summary

Based on findings in animals, ALOPRIM may cause fetal harm when administered to a pregnant woman. Adverse developmental outcomes have been described in exposed animals (see Data). Allopurinol and its metabolite oxypurinol have been shown to cross the placenta following administration of maternal allopurinol.

Available limited published data on allopurinol use in pregnant women do not demonstrate a clear pattern or increase in frequency of adverse developmental outcomes. Among approximately 50 pregnancies described in published literature, 2 infants with major congenital malformations have been reported with following maternal allopurinol exposure. Advise pregnant women of the potential risk to a fetus.

All pregnancies have a background risk of birth defect, loss, or other adverse outcomes. The estimated background risk of major birth defects and miscarriage for the indicated population is unknown. In the U.S. general population, the estimated background risk of major birth defects and miscarriage in clinically recognized pregnancies is 2% to 4% and 15% to 20%, respectively.

Data

Animal Data

There was no evidence of fetotoxicity or teratogenicity in rats or rabbits treated during the period of organogenesis with oral allopurinol at doses up to 200 mg/kg/day and up to 100 mg/kg/day, respectively (about three times the human dose on a mg/m^2 basis). However, there is a published report in pregnant mice that single intraperitoneal doses of 50 or 100 mg/kg (about 1/3 or 3/4 the human dose on a mg/m^2 basis) of allopurinol on gestation days 10 or 13 produced significant increases in fetal deaths and teratogenic effects (cleft palate, harelip, and digital defects). It is uncertain whether these findings represented a fetal effect or an effect secondary to maternal toxicity. In another published study with no reported maternal toxicity, allopurinol administered orally at 15 or 45 mg/kg to pregnant rats during organogenesis caused embryonic resorptions, growth retardation, decreased fetal weight, and skeletal, liver, kidney, and brain abnormalities. In rats, maternal treatment with allopurinol in normoxic pregnancy has been shown to increase the cardiac protein levels of sarcoplasmic/endoplasmic reticulum calcium ATPase 2 (SERCA2a) in the adult male offspring. The mechanism underlying this effect is not understood. However, this effect was not matched by an increase in left ventricular end diastolic pressure or sympathetic dominance in hearts of adult male offspring of normoxic pregnancy treated with allopurinol.

8.2 Lactation

Risk Summary

Allopurinol and oxypurinol are present in human milk. Based on information from a single case report, allopurinol and its active metabolite, oxypurinol, were detected in the milk of a mother at five weeks postpartum at an estimated relative infant dose of 0.14 and 0.2 mg/kg of allopurinol and between 7.2 to 8 mg/kg of oxypurinol daily. There was no report of effects of allopurinol on the breastfed infant or on milk production. Because of the potential for serious adverse reactions in a breastfed child, advise women not to breastfeed during treatments with ALOPRIM and for one week after the last dose.

8.4 Pediatric Use

The safety and effectiveness of ALOPRIM have been established in approximately 200 pediatric patients. The efficacy and safety profile observed in this patient population were similar to that observed in adults.

8.5 Geriatric Use

Clinical studies of ALOPRIM did not include sufficient numbers of patients 65 years and older to determine whether they respond differently than younger patients.

8.6 Renal Impairment

Allopurinol and its primary active metabolite, oxypurinol, are eliminated by the kidneys [see Clinical Pharmacology (12.3)]. Therefore, changes in renal function will likely increase allopurinal and oxypurinol exposure. In patients with decreased renal function, or who have concurrent illnesses that can affect renal function such as hypertension and diabetes mellitus, perform periodic laboratory parameters of renal function, particularly BUN and serum creatinine or creatinine clearance, should be performed.

In patients with severely impaired renal function or decreased urate clearance, the half-life of oxypurinol in the plasma is greatly prolonged. Reduce the dose of ALOPRIM in patients with creatinine clearance ≤ 20 mL/min [see Dosage and Administration (2.2)]. Patients should be treated with the lowest effective dose, in order to minimize possible side effects.

10 OVERDOSAGE

In the management of overdosage, there is no specific antidote for ALOPRIM. Both allopurinol and oxypurinol are dialyzable; however, the usefulness of hemodialysis or peritoneal dialysis in the management of an overdose of ALOPRIM is unknown.

11 DESCRIPTION

ALOPRIM (allopurinol) for Injection, a xanthine oxidase inhibitor, is a sterile, white, lyophilized powder or cake, in a single-dose vial for reconstitution. Each vial contains 500 mg of allopurinol equivalent to 580.7 mg of allopurinol sodium and 148 mg of sodium hydroxide as a solubilizer. Sodium hydroxide is also used as a pH adjuster. ALOPRIM (allopurinol) for Injection contains no preservatives.

Allopurinol is a xanthine oxidase inhibitor. The chemical name for allopurinol sodium is 1,5-dihydro-4H-pyrazolo[3,4-d]pyrimidin-4-one monosodium salt. It is a white amorphous mass with a molecular weight of 158.09 and molecular formula C5H3N4NaO. The structural formula is:

The pKa of allopurinol sodium is 9.31.

12 CLINICAL PHARMACOLOGY

12.1 Mechanism of Action

Allopurinol is a structural analogue of the natural purine base, hypoxanthine. Allopurinol and its oxypurinol metabolite inhibitor xanthine oxidase, the enzyme responsible for the conversion of hypoxanthine to xanthine and of xanthine to uric acid, the end product of purine metabolism in humans. Allopurinol does not disrupt the biosynthesis of purines.

The action of oral allopurinol differs from that of uricosuric agents, which lower the serum uric acid level by increasing urinary excretion of uric acid. Allopurinol reduces both the serum and urinary uric acid levels by inhibiting the formation of uric acid. The use of allopurinol to block the formation of urates avoids the hazard of increased renal excretion of uric acid posed by uricosuric drugs.

12.2 Pharmacodynamics

Allopurinol reduces the production of uric acid by inhibiting the biochemical reactions immediately preceding its formation in a dose dependent manner. The pharmacological action of allopurinol is generally believed to be mediated by its oxypurinol metabolite.

Effect on Hypoxanthine and Xanthine

Reutilization of both hypoxanthine and xanthine for nucleotide and nucleic acid synthesis is markedly enhanced when their oxidations are inhibited by allopurinol and oxypurinol. This reutilization does not disrupt normal nucleic acid anabolism because feedback inhibition is an integral part of purine biosynthesis. As a result of xanthine oxidase inhibition, the serum concentration of hypoxanthine plus xanthine in patients receiving allopurinol for treatment of hyperuricemia is usually in the range of 0.3 to 0.4 mg/dL compared to a normal level of approximately 0.15 mg/dL. A maximum of 0.9 mg/dL of these oxypurines has been reported when the serum urate was lowered to less than 2 mg/dL by high doses of allopurinol. These values are far below the saturation levels, at which point their precipitation would be expected to occur (above 7 mg/dL). The increased xanthine and hypoxanthine in the urine in patients who were treated with oral allopurinol have not been accompanied by problems of nephrolithiasis; however, there are isolated case reports of xanthine crystalluria.

Drug Interaction Studies

Fluorouracil

Based on non-clinical data, allopurinol may decrease anti-tumor activity due to suppression of phosphorylation of 5-fluorouracil.

Pegloticase

Concomitant use of ALOPRIM and pegloticase may potentially blunt the rise of serum uric acid levels required for monitoring the safe use of pegloticase.

Cytotoxic Agents

Enhanced bone marrow suppression by cyclophosphamide and other cytotoxic agents has been reported among patients with neoplastic disease, except leukemia, in the presence of allopurinol.

Thiazide Diuretics

Reports that the concomitant administration of allopurinol and thiazide diuretics contributed to increased allopurinol toxicity were reviewed; however, a causal mechanism or cause-and-effect relationship was not found.

12.3 Pharmacokinetics

Following single 100 mg and 300 mg intravenous and oral administration of ALOPRIM, the relative intravenous Cmax was approximately 3-fold and 3.8-fold and AUC0-inf was approximately 1.9-fold higher for allopurinol at both dosages, respectively. The relative intravenous oxypurinol Cmax and AUC0-inf was approximately 1 compaired to oral administration at both dosages.

The Cmax and AUC0- inf for both allopurinol and oxypurinol following intravenous administration of ALOPRIM were dose proportional in the dose range of 100 to 300 mg.

Distribution

The steady-state allopurinol volume of distribution (mean ± S.D.) is approximately 0.87 ± 0.13 L/Kg following intravenous adminstration.

Elimination

The half-life (mean ± S.D.) of allopurinol and oxypurinol are approximately 1.21 ± 0.33 and 23.5 ± 4.5 hours following intravenous administration, respectively. The net renal clearance of oxypurinol about 30 mL/min.

Metabolism

Allopurinol is a weak CYP1A2 inhibitor. Allopurinol is rapidly eliminated from the systemic circulation primarily via oxidative metabolism to oxypurinol.

The oxypurinol (alloxanthine) metabolite is also a xanthine oxidase inhibitor and is present in systemic circulation in much higher concentrations and for a much longer period than allopurinol. In general, the ratio of the area under the plasma concentration vs time curve (AUC0-inf) between oxypurinol and allopurinol was in the magnitude of 30 to 40.

Excretion

Approximately 12% of an allopurinol intravenous dose was excreted unchanged, 76% excreted as oxypurinol, and the remaining dose excreted as riboside conjugates in the urine. Oxypurinol was primarily eliminated unchanged in urine by glomerular filtration and tubular reabsorption.

Capecitabine

Concomitant use with allopurinol may decrease concentration of capecitabine’s active metabolites, which may decrease capecitabine efficacy.

Cyclosporine

Concomitant use of allopurinol increases cyclosporine concentrations which may increase the risk of adverse reactions.

Mercaptopurine or Azathioprine

Allopurinol inhibits xanthine oxidase mediated metabolism of mercaptopurine and azathioprine. Concomitant use of allopurinol increases the exposure of either mercaptopurine or azathioprine which may increase the risk of their adverse reactions including myelosuppression.

Theophylline

Concomitant use of allopurinol doses greater than or equal to 600 mg/day may decrease the clearance of theophylline.

Uricosuric Agents

Uricosuric agents increase the excretion of the active allopurinol metabolite oxypurinol. Concomitant use with uricosuric agents decreases oxypurinol exposure which may reduce the inhibition of xanthine oxidase by oxypurinol and increases the urinary excretion of uric acid.

Warfarin

Allopurinol may inhibit the metabolism of warfarin, possibly enhancing its anticoagulant effect.

12.5 Pharmacogenomics

The HLA-B*58:01 allele is a genetic marker for severe skin reactions indicative of hypersensitivity to allopurinol [see Warnings and Precautions (5.1)]. The frequency of the HLA-B*58:01 allele ranges from 8 to 10% in Han Chinese populations, about 8% in Thai populations, and about 6% in Korean populations based upon published literature and available databases. The frequency of the HLA-B*58:01 allele is about 4% in Blacks, about 1-2 % in indigenous peoples of the Americas and Hispanic populations, and <1% in people from European descent and Japanese.

13 NONCLINICAL TOXICOLOGY

13.1 Carcinogenesis, Mutagenesis, Impairment of Fertility

Allopurinol was administered at doses up to 20 mg/kg/day to mice and rats for the majority of their life span. No evidence of carcinogenicity was seen in either mice or rats (at doses about 1/6 or 1/3 the recommended human dose on a mg/m^2 basis, respectively).

Allopurinol administered intravenously to rats (50 mg/kg) was not incorporated into rapidly replicating intestinal DNA. No evidence of clastogenicity was observed in an in vivo micronucleus test in rats, or in lymphocytes taken from patients treated with allopurinol (mean duration of treatment 40 months), or in an in vitro assay with human lymphocytes.

Allopurinol oral doses of 20 mg/kg/day had no effect on male or female fertility in rats or rabbits (about 1/3 or 1/2 the human dose on a mg/m^2 basis, respectively).

14 CLINICAL STUDIES

A compassionate use trial of ALOPRIM conducted in the United States from 1977 through 1989 included 718 evaluable patients with malignancies requiring treatment with cytotoxic chemotherapy who were unable to ingest or retain oral medication. Of these patients, 411 had established hyperuricemia and 307 had normal serum urate levels at the time that treatment was initiated. Normal serum uric acid levels were achieved in 68% of the former (reduction of serum uric acid was documented in 93%), and were maintained throughout chemotherapy in 97% of the latter. Because of the study design, it was not possible to assess the impact of the treatment with ALOPRIM on the clinical outcome of the patient groups.

16 HOW SUPPLIED/STORAGE AND HANDLING

ALOPRIM (allopurinol) for Injection is supplied in 30 mL flint glass single-dose vials. Each vial contains 500 mg of allopurinol as a sterile, white, lyophilized powder or cake for reconstitution.

NDC 67457-187-50
One vial per carton

Store at 20°C to 25°C (68°F to 77°F); excursions permitted to 15°C to 30°C (59°F to 86°F) [see USP Controlled Room Temperature].

17 PATIENT COUNSELING INFORMATION

Skin Rash and Hypersensitivity

Inform patients that ALOPRIM may increase the risk of serious and sometimes fatal dermatologic reactions, including toxic epidermal necrolysis (TEN), Stevens-Johnson syndrome (SJS), and drug reaction with eosinophilia and systemic symptoms (DRESS). Instruct the patient to be alert for skin rash, blisters, fever or other signs and symptoms of these hypersensitivity reactions. Advise patients to stop the ALOPRIM immediately if they develop any type of rash and seek medical attention [see Warnings and Precautions (5.1)].

Renal Function Impairment

Advise patients to stay well hydrated (e.g., 2 liters of liquid per day) while taking ALOPRIM [see Warnings and Precautions (5.2)].

Hepatotoxicity

Advise patients of the risk of hepatoxicity and to report any signs and symptoms of liver failure, including jaundice, pruritus, bleeding, bruising, or anorexia to their healthcare provider [see Warnings and Precautions (5.3)].

Myelosuppression

Advise patients of the risk of myelosuppression and to report any signs and symptoms of infection, fever, bleeding, shortness of breath, or significant fatigue to their healthcare provider [see Warnings and Precautions (5.4)].

Drowsiness

Inform patients that drowsiness has been reported in patients taking ALOPRIM and to be cautious when engaging in activities where alertness is mandatory [see Warnings and Precautions (5.5)].

Pregnancy

Advise pregnant women of the potential risk to a fetus. Advise women to notify their healthcare provider if they become pregnant or intend to become pregnant during treatment with Aloprim [see Use in Specific Populations (8.1)].

Lactation

Advise women not to breastfeed during treatment with ALOPRIM for one week after the last dose. [see Use in Specific Populations (8.2)].

Manufactured for:
Mylan Institutional LLC
Morgantown, WV 26505 U.S.A.

Manufactured by:
NerPharMa Srl
V.le Pasteur 10
20014 Nerviano (MI), Italy

MI:ALOPIJ:R9

P2119476

ALOPRIM is a registered trademark of Mylan Teoranta, a Viatris Company.

PRINCIPAL DISPLAY PANEL – 500 mg/vial

NDC 67457-187-50

ALOPRIM®
(allopurinol)
for Injection
500 mg/vial

For Intravenous
Infusion

Sterile

Single-Dose Vial. Discard unused portion.

Rx only

Each vial contains 500 mg of
allopurinol equivalent to 580.7 mg of
allopurinol sodium and 148 mg of
sodium hydroxide as a solubilizer.

Sodium hydroxide is also used as a
pH adjuster.

Preparation of Solution:
Inject 25 mL Sterile Water for Injection,
USP into vial. Swirl vial until solution
results. The reconstituted solution
contains allopurinol at a concentration
of 20 mg/mL. The solution should be
stored at 20°C to 25°C (68°F to 77°F)
and administration should be completed
within 10 hours after reconstitution.
Further dilution is required before
intravenous administration.

Recommended Dosage: See
prescribing information.

Store at 20°C to 25°C (68°F to 77°F);
excursions permitted to 15ºC to 30ºC
(59ºF to 86ºF) [see USP Controlled
Room Temperature].

ALOPRIM is a registered trademark of
Mylan Teoranta, a Viatris Company.

Manufactured for:
Mylan Institutional LLC
Morgantown, WV 26505 U.S.A.

Made in Italy

MI:187:1C:R9

Mylan.com